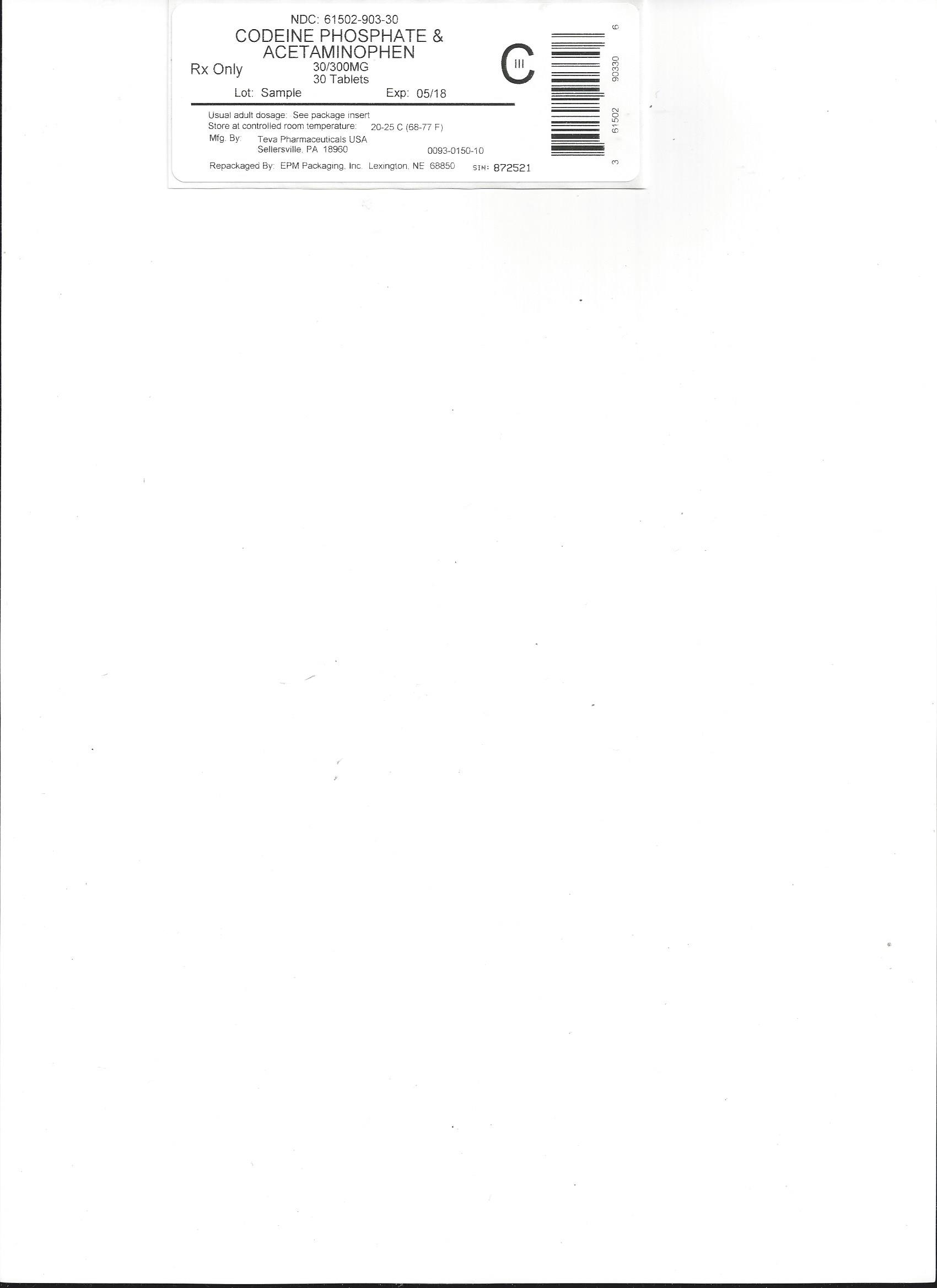 DRUG LABEL: ACETAMINOPHEN AND CODEINE PHOSPHATE
NDC: 61502-903 | Form: TABLET
Manufacturer: EPM Packaging Inc
Category: prescription | Type: HUMAN PRESCRIPTION DRUG LABEL
Date: 20160127
DEA Schedule: CIII

ACTIVE INGREDIENTS: ACETAMINOPHEN 300 mg/1 1; CODEINE PHOSPHATE 30 mg/1 1

BOXED WARNING

Hepatotoxicity
Acetaminophen has been associated with cases of acute liver failure, at times resulting in liver
transplant and death. Most of the cases of liver injury are associated with the use of
acetaminophen at doses that exceed 4000 milligrams per day, and often involve more than one
acetaminophen-containing product.
WARNING: Death Related to Ultra-Rapid Metabolis m of Codeine to Morphine
Respiratory depression and death have occurred in children who received codeine following
tonsillectomy and/or adenoidectomy and had evidence of being ultra-rapid metabolizers of
codeine due to a CYP2D6 polymorphism.

DESCRIPTION

ACETAMINOPHEN AND CODEINE PHOSPHATE TABLETS, USP CIII
Rx only

Acetaminophen and codeine are supplied in tablet form for oral administration.
Acetaminophen, USP, 4'-hydroxyacetanilide, a slightly bitter, white, odorless, crystalline powder, is a
non-opiate, non-salicylate analgesic and antipyretic. It has the following structural formula:
C H NO M.W. 151.16
Codeine phosphate, USP, 7,8-didehydro-4,5α-epoxy-3-methoxy-17-methylmorphinan-6α-ol phosphate
(1:1) (salt) hemihydrate, a white crystalline powder, is a narcotic analgesic and antitussive. It has the
following structural formula:
8 9 2
C H NO •H PO •1/2H O M.W. 406.37
Each tablet contains:
acetaminophen, USP...........................300 mg
codeine phosphate, USP.......................15 mg
(Warning: May be habit forming)
OR
acetaminophen, USP...........................300 mg
codeine phosphate, USP....................... 30 mg
(Warning: May be habit forming)
OR
acetaminophen, USP...........................300 mg
codeine phosphate, USP....................... 60 mg
(Warning: May be habit forming)
In addition, each tablet contains the following inactive ingredients: corn starch, colloidal silicon
dioxide, croscarmellose sodium, magnesium stearate, and microcrystalline cellulose. The 300 mg/60
mg strength tablets also contain crospovidone, povidone, pregelatinized starch, and stearic acid.
CLINICAL PHARMACOLOGY
This product combines the analgesic effects of a centrally acting analgesic, codeine, with a
peripherally acting analgesic, acetaminophen.
Pharmacokinetics
The behavior of the individual components is described below.
Codeine
Codeine is readily absorbed from the gastrointestinal tract. It is rapidly distributed from the
intravascular spaces to the various body tissues, with preferential uptake by parenchymatous organs
such as the liver, spleen and kidney. Codeine crosses the blood-brain barrier, and is found in fetal tissue
and breast milk. The plasma concentration does not correlate with brain concentration or relief of pain;
however, codeine is not bound to plasma proteins and does not accumulate in body tissues.
The plasma half-life is about 2.9 hours. The elimination of codeine is primarily via the kidneys, and
about 90% of an oral dose is excreted by the kidneys within 24 hours of dosing. The urinary secretion
products consist of free and glucuronide conjugated codeine (about 70%), free and conjugated
norcodeine (about 10%), free and conjugated morphine (about 10%), normorphine (4%), and
hydrocodone (1%). The remainder of the dose is excreted in the feces.
18 21 3 3 4 2
At therapeutic doses, the analgesic effect reaches a peak within 2 hours and persists between 4 and 6
hours.
See OVERDOSAGE for toxicity information.
Acetaminophen
Acetaminophen is rapidly absorbed from the gastrointestinal tract and is distributed throughout most
body tissues. The plasma half-life is 1.25 to 3 hours, but may be increased by liver damage and
following overdosage. Elimination of acetaminophen is principally by liver metabolism (conjugation)
and subsequent renal excretion of metabolites. Approximately 85% of an oral dose appears in the urine
within 24 hours of administration, most as the glucuronide conjugate, with small amounts of other
conjugates and unchanged drug.
See OVERDOSAGE for toxicity information.
INDICATIONS AND USAGE
Acetaminophen and codeine phosphate tablets are indicated for the relief of mild to moderately severe
pain.

CONTRAINDICATIONS

Codeine-containing products are contraindicated for postoperative pain management in children who
have undergone tonsillectomy and/or adenoidectomy.
This product should not be administered to patients who have previously exhibited hypersensitivity to
codeine or acetaminophen.

WARNINGS

In the presence of head injury or other intracranial lesions, the respiratory depressant effects of codeine
and other narcotics may be markedly enhanced, as well as their capacity for elevating cerebrospinal
fluid pressure. Narcotics also produce other CNS depressant effects, such as drowsiness, that may
further obscure the clinical course of the patients with head injuries.
Codeine or other narcotics may obscure signs on which to judge the diagnosis or clinical course of
patients with acute abdominal conditions.
Codeine is habit-forming and potentially abusable. Consequently, the extended use of this product is not
recommended.
Hepatotoxicity
Acetaminophen has been associated with cases of acute liver failure, at times resulting in liver
transplant and death. Most of the cases of liver injury are associated with the use of acetaminophen at
doses that exceed 4000 milligrams per day, and often involve more than one acetaminophen-containing
product. The excessive intake of acetaminophen may be intentional to cause self-harm or unintentional
as patients attempt to obtain more pain relief or unknowingly take other acetaminophen-containing
products.
The risk of acute liver failure is higher in individuals with underlying liver disease and in individuals
who ingest alcohol while taking acetaminophen.
Instruct patients to look for acetaminophen or APAP on package labels and not to use more than one
product that contains acetaminophen. Instruct patients to seek medical attention immediately upon
ingestion of more than 4000 milligrams of acetaminophen per day, even if they feel well.
Serious Skin Reactions
Rarely, acetaminophen may cause serious skin reactions such as acute generalized exanthematous
pustulosis (AGEP), Stevens-Johnson syndrome (SJS), and toxic epidermal necrolysis (TEN), which can
be fatal. Patients should be informed about the signs of serious skin reactions, and use of the drug
should be discontinued at the first appearance of skin rash or any other sign of hypersensitivity.
Death Related to Ultra-Rapid Metabolis m of Codeine to Morphine
Respiratory depression and death have occurred in children who received codeine in the post-operative
period following tonsillectomy and/or adenoidectomy and had evidence of being ultra-rapid
metabolizers of codeine (i.e., multiple copies of the gene for cytochrome P450 isoenzyme 2D6 or high
morphine concentrations). Deaths have also occurred in nursing infants who were exposed to high
levels of morphine in breast milk because their mothers were ultra-rapid metabolizers of codeine [see
PRECAUTIONS, Nurs ing Mothers ].
Some individuals may be ultra-rapid metabolizers because of a specific CYP2D6 genotype (gene
duplications denoted as *1/*1xN or *1/*2xN). The prevalence of this CYP2D6 phenotype varies widely
and has been estimated at 0.5 to 1% in Chinese and Japanese, 0.5 to 1% in Hispanics, 1 to 10% in
Caucasians, 3% in African Americans, and 16 to 28% in North Africans, Ethiopians, and Arabs. Data are
not available for other ethnic groups. These individuals convert codeine into its active metabolite,
morphine, more rapidly and completely than other people. This rapid conversion results in higher than
expected serum morphine levels. Even at labeled dosage regimens, individuals who are ultra-rapid
metabolizers may have life-threatening or fatal respiratory depression or experience signs of overdose
(such as extreme sleepiness, confusion, or shallow breathing) [see OVERDOSAGE].
Children with obstructive sleep apnea who are treated with codeine for post-tonsillectomy and/or
adenoidectomy pain may be particularly sensitive to the respiratory depressant effects of codeine that
has been rapidly metabolized to morphine. Codeine-containing products are contraindicated for postoperative
pain management in all pediatric patients undergoing tonsillectomy and/or adenoidectomy [see

CONTRAINDICATIONS].
When prescribing codeine-containing products, healthcare providers should choose the lowest
effective dose for the shortest period of time and inform patients and caregivers about these risks and
the signs of morphine overdose [see OVERDOSAGE].
Hypers ens itivity/Anaphylaxis
There have been postmarketing reports of hypersensitivity and anaphylaxis associated with use of
acetaminophen. Clinical signs included swelling of the face, mouth, and throat, respiratory distress,
urticaria, rash, pruritus, and vomiting. There were infrequent reports of life-threatening anaphylaxis
requiring emergency medical attention. Instruct patients to discontinue acetaminophen and codeine
phosphate tablets, USP immediately and seek medical care if they experience these symptoms. Do not
prescribe acetaminophen and codeine phosphate tablets, USP for patients with acetaminophen allergy.
Alcohol Information
Chronic heavy alcohol abusers may be at increased risk of liver toxicity from excessive acetaminophen
use, although reports of this event are rare. Reports almost invariably involve cases of severe chronic
alcoholics and the dosages of acetaminophen most often exceed recommended doses and often involve
substantial overdose. Professionals should alert their patients who regularly consume large amounts of
alcohol not to exceed recommended doses of acetaminophen.

PRECAUTIONS

In the presence of head injury or other intracranial lesions, the respiratory depressant effects of codeine
and other narcotics may be markedly enhanced, as well as their capacity for elevating cerebrospinal
fluid pressure. Narcotics also produce other CNS depressant effects, such as drowsiness, that may
further obscure the clinical course of the patients with head injuries.
Codeine or other narcotics may obscure signs on which to judge the diagnosis or clinical course of
patients with acute abdominal conditions.
Codeine is habit-forming and potentially abusable. Consequently, the extended use of this product is not
recommended.
Hepatotoxicity
Acetaminophen has been associated with cases of acute liver failure, at times resulting in liver
transplant and death. Most of the cases of liver injury are associated with the use of acetaminophen at
doses that exceed 4000 milligrams per day, and often involve more than one acetaminophen-containing
product. The excessive intake of acetaminophen may be intentional to cause self-harm or unintentional
as patients attempt to obtain more pain relief or unknowingly take other acetaminophen-containing
products.
The risk of acute liver failure is higher in individuals with underlying liver disease and in individuals
who ingest alcohol while taking acetaminophen.
Instruct patients to look for acetaminophen or APAP on package labels and not to use more than one
product that contains acetaminophen. Instruct patients to seek medical attention immediately upon
ingestion of more than 4000 milligrams of acetaminophen per day, even if they feel well.
Serious Skin Reactions
Rarely, acetaminophen may cause serious skin reactions such as acute generalized exanthematous
pustulosis (AGEP), Stevens-Johnson syndrome (SJS), and toxic epidermal necrolysis (TEN), which can
be fatal. Patients should be informed about the signs of serious skin reactions, and use of the drug
should be discontinued at the first appearance of skin rash or any other sign of hypersensitivity.
Death Related to Ultra-Rapid Metabolis m of Codeine to Morphine
Respiratory depression and death have occurred in children who received codeine in the post-operative
period following tonsillectomy and/or adenoidectomy and had evidence of being ultra-rapid
metabolizers of codeine (i.e., multiple copies of the gene for cytochrome P450 isoenzyme 2D6 or high
morphine concentrations). Deaths have also occurred in nursing infants who were exposed to high
levels of morphine in breast milk because their mothers were ultra-rapid metabolizers of codeine [see
PRECAUTIONS, Nurs ing Mothers ].
Some individuals may be ultra-rapid metabolizers because of a specific CYP2D6 genotype (gene
duplications denoted as *1/*1xN or *1/*2xN). The prevalence of this CYP2D6 phenotype varies widely
and has been estimated at 0.5 to 1% in Chinese and Japanese, 0.5 to 1% in Hispanics, 1 to 10% in
Caucasians, 3% in African Americans, and 16 to 28% in North Africans, Ethiopians, and Arabs. Data are
not available for other ethnic groups. These individuals convert codeine into its active metabolite,
morphine, more rapidly and completely than other people. This rapid conversion results in higher than
expected serum morphine levels. Even at labeled dosage regimens, individuals who are ultra-rapid
metabolizers may have life-threatening or fatal respiratory depression or experience signs of overdose
(such as extreme sleepiness, confusion, or shallow breathing) [see OVERDOSAGE].
Children with obstructive sleep apnea who are treated with codeine for post-tonsillectomy and/or
adenoidectomy pain may be particularly sensitive to the respiratory depressant effects of codeine that
has been rapidly metabolized to morphine. Codeine-containing products are contraindicated for postoperative
pain management in all pediatric patients undergoing tonsillectomy and/or adenoidectomy [see

CONTRAINDICATIONS].
When prescribing codeine-containing products, healthcare providers should choose the lowest
effective dose for the shortest period of time and inform patients and caregivers about these risks and
the signs of morphine overdose [see OVERDOSAGE].
Hypers ens itivity/Anaphylaxis
There have been postmarketing reports of hypersensitivity and anaphylaxis associated with use of
acetaminophen. Clinical signs included swelling of the face, mouth, and throat, respiratory distress,
urticaria, rash, pruritus, and vomiting. There were infrequent reports of life-threatening anaphylaxis
requiring emergency medical attention. Instruct patients to discontinue acetaminophen and codeine
phosphate tablets, USP immediately and seek medical care if they experience these symptoms. Do not
prescribe acetaminophen and codeine phosphate tablets, USP for patients with acetaminophen allergy.
Alcohol Information
Chronic heavy alcohol abusers may be at increased risk of liver toxicity from excessive acetaminophen
use, although reports of this event are rare. Reports almost invariably involve cases of severe chronic
alcoholics and the dosages of acetaminophen most often exceed recommended doses and often involve
substantial overdose. Professionals should alert their patients who regularly consume large amounts of
alcohol not to exceed recommended doses of acetaminophen.

ADVERSE REACTIONS

The most frequently reported adverse reactions are drowsiness, lightheadedness, dizziness, sedation,
shortness of breath, nausea and vomiting. These effects seem to be more prominent in ambulatory than in
non-ambulatory patients, and some of these adverse reactions may be alleviated if the patient lies down.
Other adverse reactions include allergic reactions, euphoria, dysphoria, constipation, abdominal pain,
pruritus, rash, thrombocytopenia, agranulocytosis.
At higher doses codeine has most of the disadvantages of morphine including respiratory depression.
DRUG ABUSE AND DEPENDENCE
Controlled Subs tance
Acetaminophen and codeine phosphate tablets are classified as a Schedule III controlled substance.
Abus e and Dependence
Codeine can produce drug dependence of the morphine type and, therefore, has the potential for being
abused. Psychological dependence, physical dependence, and tolerance may develop upon repeated
administration and it should be prescribed and administered with the same degree of caution appropriate
to the use of other oral narcotic medications.

OVERDOSAGE

Following an acute overdosage, toxicity may result from codeine or acetaminophen.
Signs and Symptoms
Toxicity from codeine poisoning includes the opioid triad of: pinpoint pupils, depression of respiration,
and loss of consciousness. Convulsions may occur.
In acetaminophen overdosage: dose-dependent, potentially fatal hepatic necrosis is the most serious
adverse effect. Renal tubular necrosis, hypoglycemic coma and coagulation defects may also occur.
Early symptoms following a potentially hepatotoxic overdose may include: nausea, vomiting,
diaphoresis and general malaise. Clinical and laboratory evidence of hepatic toxicity may not be
apparent until 48 to 72 hours post-ingestion.
Treatment
A single or multiple drug overdose with acetaminophen and codeine is a potentially lethal polydrug
overdose, and consultation with a regional poison control center is recommended. Immediate treatment
includes support of cardiorespiratory function and measures to reduce drug absorption.
Oxygen, intravenous fluids, vasopressors, and other supportive measures should be employed as
indicated. Assisted or controlled ventilation should also be considered. For respiratory depression due
to overdosage or unusual sensitivity to codeine, parenteral naloxone is a specific and effective
antagonist.
Gastric decontamination with activated charcoal should be administered just prior to N-acetylcysteine
(NAC) to decrease systemic absorption if acetaminophen ingestion is known or suspected to have
occurred within a few hours of presentation. Serum acetaminophen levels should be obtained
immediately if the patient presents 4 hours or more after ingestion to assess potential risk of
hepatotoxicity; acetaminophen levels drawn less than 4 hours post-ingestion may be misleading. To
obtain the best possible outcome, NAC should be administered as soon as possible where impending or
evolving liver injury is suspected. Intravenous NAC may be administered when circumstances preclude
oral administration.
Vigorous supportive therapy is required in severe intoxication. Procedures to limit the continuing
absorption of the drug must be readily performed since the hepatic injury is dose dependent and occurs
early in the course of intoxication.

DOSAGE AND ADMINISTRATION

Dosage should be adjusted according to severity of pain and response of the patient.
The usual adult dosage is:
Single Doses (range) Maximum 24 Hour Dose
Codeine Phosphate 15 mg to 60 mg 360 mg
Acetaminophen 300 mg to 1000 mg 4000 mg
The usual dose of codeine phosphate in children is 0.5 mg/kg.
Doses may be repeated up to every 4 hours.
The prescriber must determine the number of tablets per dose, and the maximum number of tablets per
24 hours based upon the above dosage guidance. This information should be conveyed in the
prescription.
It should be kept in mind, however, that tolerance to codeine can develop with continued use and that the
incidence of untoward effects is dose related. Adult doses of codeine higher than 60 mg fail to give
commensurate relief of pain but merely prolong analgesia and are associated with an appreciably
increased incidence of undesirable side effects. Equivalently high doses in children would have similar
effects.

HOW SUPPLIED
Acetaminophen and codeine phosphate tablets USP (white, round, unscored):
Acetaminophen and codeine phosphate tablets USP (white, round, unscored):
List No. 0050, acetaminophen 300 mg and codeine phosphate 15 mg, debossed “2” on one side and
“TV”-“50” on the other side of tablet is available in bottles of 100 (NDC 0093-0050-01) tablets.
List No. 0150, acetaminophen 300 mg and codeine phosphate 30 mg, debossed “3” on one side and
“TV”-“150” on the other side of tablet is available in bottles of 100 (NDC 0093-0150-01) and 1000
(NDC 0093-0150-10) tablets.
List No. 0350, acetaminophen 300 mg and codeine phosphate 60 mg, debossed “4” on one side and
“93”-“350” on the other side of tablet is available in bottles of 100 (NDC 0093-0350-01), 500 (NDC
0093-0350-05), and 1000 (NDC 0093-0350-10) tablets.
Store at 20° to 25°C (68° to 77°F) [See USP Controlled Room Temperature]. Protect from moisture.
PROTECT FROM LIGHT
Dispense in a tight, light-resistant container as defined in the USP, with a child-resistant closure (as
required).
KEEP THIS AND ALL MEDICATIONS OUT OF THE REACH OF CHILDREN.
Distributed By:
TEVA PHARMACEUTICALS USA, INC.
North Wales, PA 19454
Rev. AI 8/2015